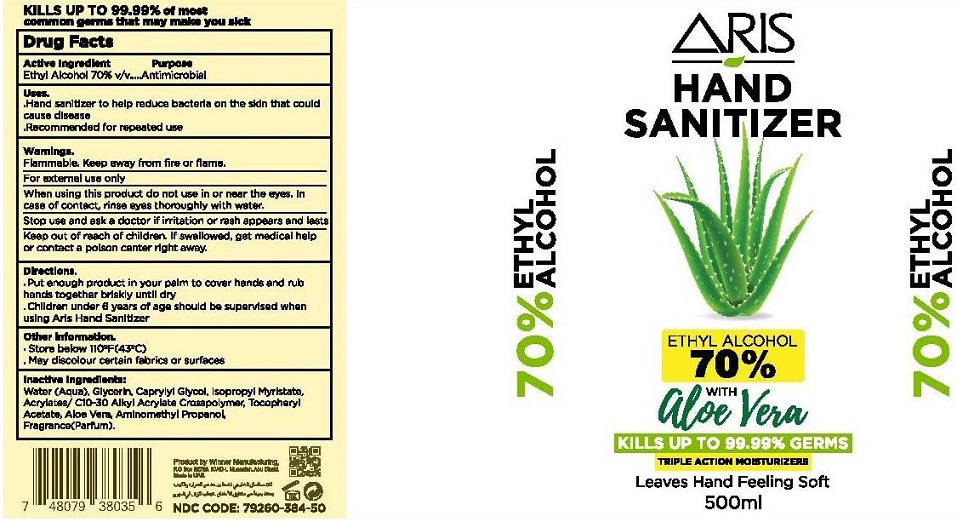 DRUG LABEL: Aris Hand Sanitizer with Aloe Vera
NDC: 79260-384 | Form: GEL
Manufacturer: WINNER MANUFACTURING
Category: otc | Type: HUMAN OTC DRUG LABEL
Date: 20200709

ACTIVE INGREDIENTS: ALCOHOL 70 mL/100 mL
INACTIVE INGREDIENTS: WATER; GLYCERIN; CAPRYLYL GLYCOL; ISOPROPYL MYRISTATE; CARBOMER INTERPOLYMER TYPE A (ALLYL SUCROSE CROSSLINKED); .ALPHA.-TOCOPHEROL ACETATE; ALOE VERA LEAF; AMINOMETHYLPROPANOL

ARIS HAND SANITIZER

Active Ingredient

Ethyl Alcohol 70% v/v

Purpose

Antimicrobial

Uses.

▪ Hand sanitizer to help reduce bacteria on the skin that could cause disease

▪ Recommended for repeated use

Warnings.

Flammable. Keep away from fire or flame

For external use only

When using this product do not use in or near the eyes. In case of contact, rinse eyes thoroughly with water.

Stop use and ask a doctor if irritation or rash appears and lasts

Keep out of reach of children. If swallowed, get medical help or contact a poison center right away.

Directions.

▪ Put enough product in your palm to cover hands and rub hands together briskly until dry.

▪ Children under 6 years of age should be supervised when using Aris Hand Sanitizer.

Other Information.

▪ Store below 110°F(43°C)

▪ May discolour certain fabrics or surfaces

Inactive Ingredients:

Water(Aqua), Glycerin, Caprylyl Glycol, Isopropyl Myristate, Acrylates/ C10-30 Alkyl Acrylate Crosspolymer,

Tocopheryl Acetate, Aloe Vera, Aminomethyl Propanol, Fragrance(Parfum).

WITH aloe vera

KILLS UP TO 99.99% GERMS

TRIPLE ACTION MOISTURIZERS

Leaves Hand Feeling Soft

KILLS UP TO 99.99% of most common germs that may make you sick